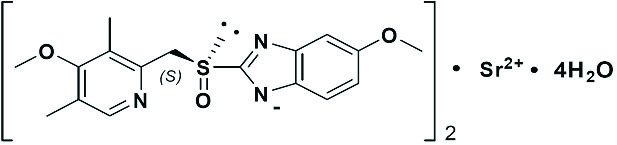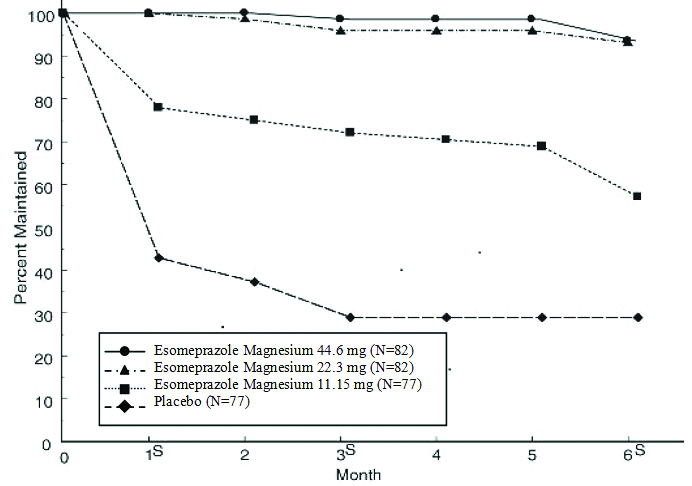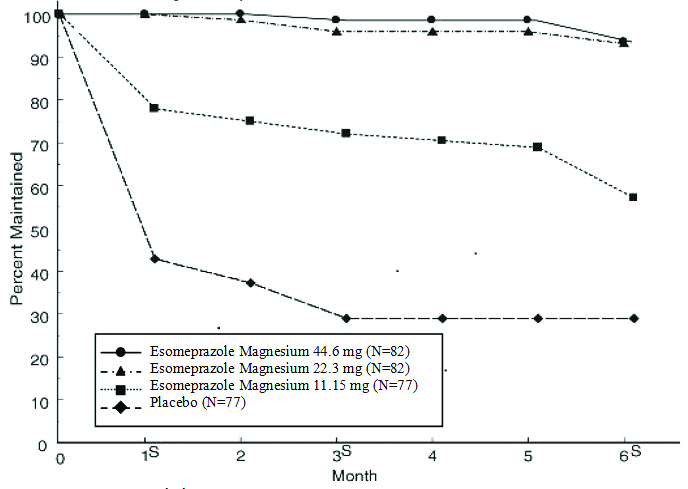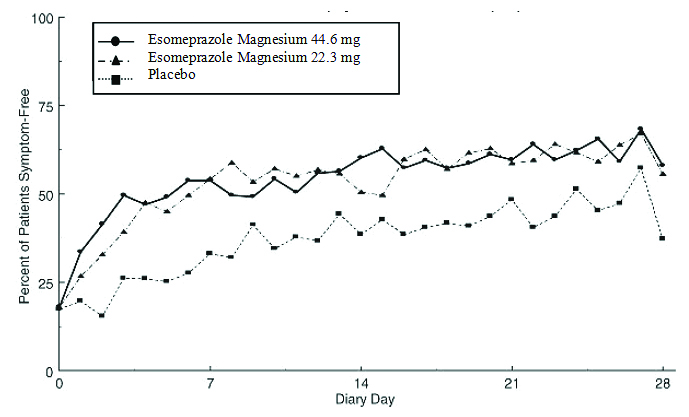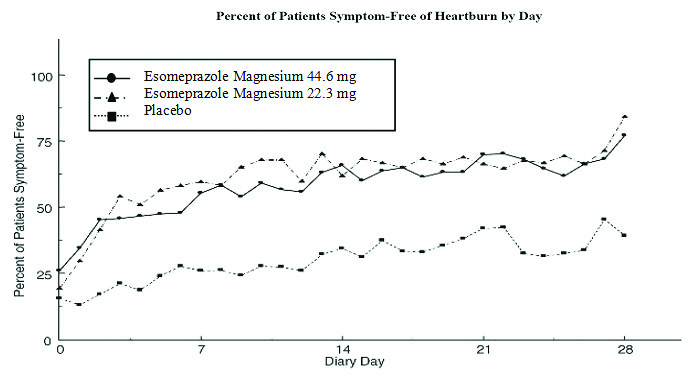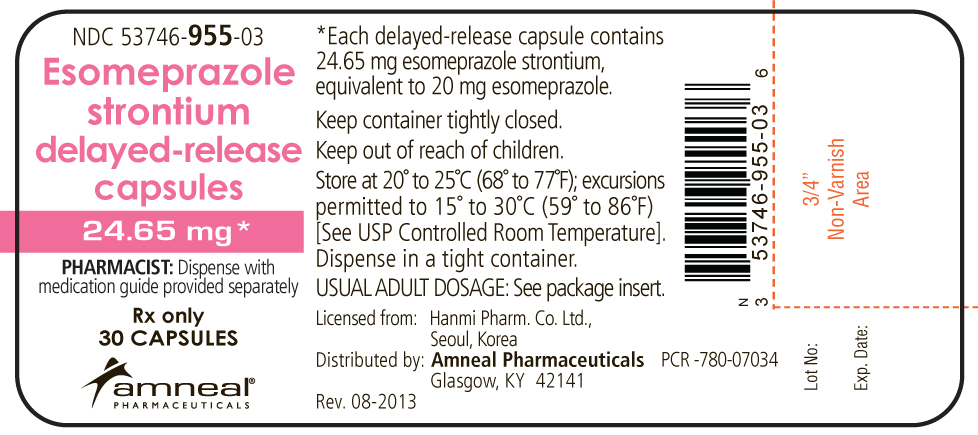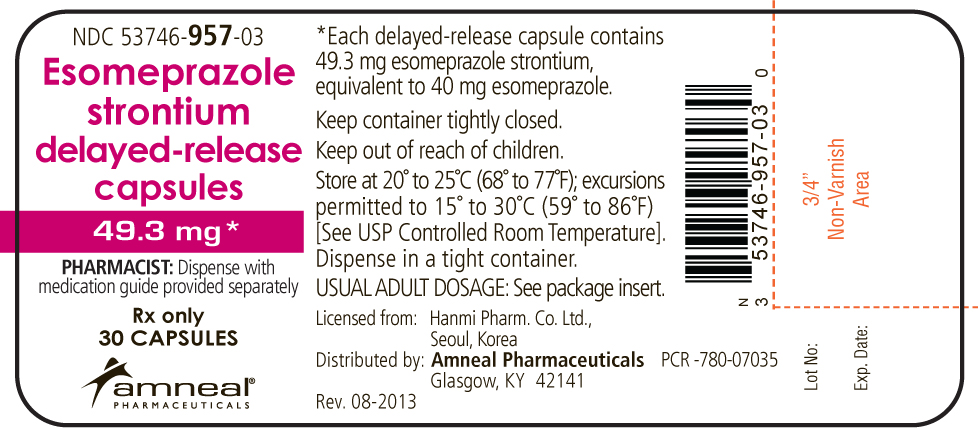 DRUG LABEL: Esomeprazole strontium
NDC: 53746-955 | Form: CAPSULE, DELAYED RELEASE
Manufacturer: Amneal Pharmaceuticals of New York LLC
Category: prescription | Type: HUMAN PRESCRIPTION DRUG LABEL
Date: 20221118

ACTIVE INGREDIENTS: ESOMEPRAZOLE STRONTIUM 20 mg/1 1
INACTIVE INGREDIENTS: CALCIUM CARBONATE; HYPROMELLOSES; METHACRYLIC ACID; POLYSORBATE 80; SUCROSE; TALC; TRIETHYL CITRATE; GELATIN; TITANIUM DIOXIDE; FERRIC OXIDE RED; GLYCERYL MONOSTEARATE; STARCH, CORN

HIGHLIGHTS OF PRESCRIBING INFORMATION

These highlights do not include all the information needed to use ESOMEPRAZOLE STRONTIUM safely and effectively. See full prescribing information for ESOMEPRAZOLE STRONTIUM.
ESOMEPRAZOLE STRONTIUM delayed-release capsules for oral use
Initial U.S. Approval: 1989 (omeprazole)

1 INDICATIONS AND USAGE

Esomeprazole strontium is a proton pump inhibitor indicated for adults for:

- Treatment of gastroesophageal reflux disease (GERD) (1.1)
- Risk reduction of NSAID-associated gastric ulcer (1.2)
- H. pylori eradication to reduce the risk of duodenal ulcer recurrence (1.3)
- Pathological hypersecretory conditions, including Zollinger-Ellison syndrome (1.4)

2 DOSAGE AND ADMINISTRATION

Indication | Dose | Frequency
Gastroesophageal Reflux Disease (GERD)
Adults | 24.65 or 49.3 mg | Once daily for 4-8 weeks
Risk Reduction of NSAID-Associated Gastric Ulcer
Adults | 24.65 or 49.3 mg | Once daily for up to 6 months
H. pylori Eradication (Triple Therapy) in Adults:
Esomeprazole strontium | 49.3 mg | Once daily for 10 days
Amoxicillin | 1000 mg | Twice daily for 10 days
Clarithromycin | 500 mg | Twice daily for 10 days
Pathological Hypersecretory Conditions
Adults | 49.3 mg | Twice daily

- See full prescribing information for full dosage and administration (2)
- Patients with severe liver impairment: do not exceed dose of 24.65 mg (2)

3 DOSAGE FORMS AND STRENGTHS

Delayed-Release Capsules (3):

- 24.65 mg of esomeprazole strontium (equivalent to 20 mg of esomeprazole)
- 49.3 mg of esomeprazole strontium (equivalent to 40 mg of esomeprazole)

4 CONTRAINDICATIONS

Patients with known hypersensitivity to proton pump inhibitors (PPIs) (angioedema and anaphylaxis have occurred) (4)

5 WARNINGS AND PRECAUTIONS

- Symptomatic response does not preclude the presence of gastric malignancy (5.1)
- Atrophic gastritis has been noted with long-term omeprazole therapy (5.2)
- PPI therapy may be associated with increased risk of Clostridium difficile associated diarrhea. (5.3)
- Avoid concomitant use of esomeprazole strontium with clopidogrel. (5.4)
- Bone Fracture: Long-term and multiple daily dose PPI therapy may be associated with an increased risk for osteoporosis-related fractures of the hip, wrist or spine. (5.5)
- Hypomagnesemia has been reported rarely with prolonged treatment with PPIs (5.6)
- Avoid concomitant use of esomeprazole strontium with St. John’s Wort or rifampin due to the potential reduction in esomeprazole levels (5.7, 7.3)
- Interactions with diagnostic investigations for Neuroendocrine Tumors: Increases in intragastric pH may result in hypergastrinemia and enterochromaffin-like cell hyperplasia and increased chromogranin A levels which may interfere with diagnostic investigations for neuroendocrine tumors. (5.8, 12.2)

6 ADVERSE REACTIONS

Most common adverse reactions in adults (≥18 years) (incidence ≥1%) are headache, diarrhea, nausea, flatulence, abdominal pain, constipation, and dry mouth (6.1)

To report SUSPECTED ADVERSE REACTIONS, contact Amneal Pharmaceuticals at 1‑877-835-5472 or FDA at 1-800-FDA-1088 or www.fda.gov/medwatch.

7 DRUG INTERACTIONS

- Antiretroviral Drugs: Use with atazanavir and nelfinavir is not recommended; if saquinavir is used with esomeprazole strontium, monitor for toxicity and consider saquinavir dose reduction (7.1)
- May interfere with drugs for which gastric pH affects bioavailability (e.g., ketoconazole, iron salts, erlotinib and digoxin). May need monitoring for digoxin toxicity (7.2)
- Combined Inhibitor of CYP 2C19 and 3A4: May raise esomeprazole levels (7.3)
- Clopidogrel: Esomeprazole strontium decreases exposure to the active metabolite of clopidogrel. (7.3)
- Cilostazol: May increase systemic exposure of cilostazol and an active metabolite. Consider dose reduction of cilostazol (7.3)
- Tacrolimus: Esomeprazole strontium may increase serum levels of tacrolimus (7.5)
- Methotrexate: Esomeprazole strontium may increase serum levels of methotrexate (7.7)

8 USE IN SPECIFIC POPULATIONS

- Pregnancy: Based on animal data, may cause fetal harm (8.1)
- Nursing Mothers: Consider discontinuing drug if nursing (8.3)
- Pediatric Use: Safety and effectiveness of esomeprazole strontium have not been established in pediatric patients. Not recommended for use in pediatric patients (8.4).
- Renal Impairment: Safety of esomeprazole strontium has not been studied in patients with severe renal impairment. Not recommended for use in patients with severe renal impairment (8.6, 12.3).

FULL PRESCRIBING INFORMATION

1 INDICATIONS AND USAGE

1.1 Treatment of Gastroesophageal Reflux Disease (GERD) in Adults

Healing of Erosive Esophagitis

Esomeprazole strontium is indicated for the short-term treatment (4 to 8 weeks) in the healing and symptomatic resolution of diagnostically confirmed erosive esophagitis. For those patients who have not healed after 4 to 8 weeks of treatment, an additional 4 to 8 week course of esomeprazole strontium may be considered.

Maintenance of Healing of Erosive Esophagitis

Esomeprazole strontium is indicated to maintain symptom resolution and healing of erosive esophagitis. Controlled studies do not extend beyond 6 months.

Symptomatic Gastroesophageal Reflux Disease

Esomeprazole strontium is indicated for short-term treatment (4 to 8 weeks) of heartburn and other symptoms associated with GERD in adults.

1.2 Risk Reduction of NSAID-Associated Gastric Ulcer in Adults

Esomeprazole strontium is indicated for the reduction in the occurrence of gastric ulcers associated with continuous NSAID therapy in patients at risk for developing gastric ulcers. Patients are considered to be at risk either due to their age (≥60) and/or documented history of gastric ulcers. Controlled studies do not extend beyond 6 months.

1.3 H. pylori Eradication to Reduce the Risk of Duodenal Ulcer Recurrence in Adults

Triple Therapy (esomeprazole strontium plus amoxicillin and clarithromycin): esomeprazole strontium, in combination with amoxicillin and clarithromycin, is indicated for the treatment of patients with H. pylori infection and duodenal ulcer disease (active or history of within the past 5 years) to eradicate H. pylori. Eradication of H. pylori has been shown to reduce the risk of duodenal ulcer recurrence [see Dosage and Administration (2) and Clinical Studies (14)].

In patients who fail therapy, susceptibility testing should be done. If resistance to clarithromycin is demonstrated or susceptibility testing is not possible, alternative antimicrobial therapy should be instituted [see Clinical Pharmacology (12.4) and the prescribing information for clarithromycin].

1.4 Pathological Hypersecretory Conditions Including Zollinger-Ellison Syndrome in Adults

Esomeprazole strontium is indicated for the long-term treatment of pathological hypersecretory conditions, including Zollinger-Ellison Syndrome.

2 DOSAGE AND ADMINISTRATION

Esomeprazole strontium is supplied as delayed-release capsules for oral administration. The recommended dosages are outlined in Table 1. Esomeprazole strontium should be taken at least one hour before meals.

The duration of proton pump inhibitor administration should be based on available safety and efficacy data specific to the defined indication and dosing frequency, as described in the prescribing information, and individual patient medical needs. Proton pump inhibitor treatment should only be initiated and continued if the benefits outweigh the risks of treatment.

Table 1: Recommended Dosage Schedule of Esomeprazole Strontium Delayed-Release Capsules
Indication | Dose | Frequency
Gastroesophageal Reflux Disease (GERD) in Adults
Healing of Erosive Esophagitis | 24.65 mga or 49.3 mgb | Once Daily for 4 to 8 Weeks*
Maintenance of Healing of Erosive Esophagitis | 24.65 mga | Once Daily**
Symptomatic Gastroesophageal Reflux Disease | 24.65 mga | Once Daily for 4 Weeks***
Risk Reduction of NSAID-Associated Gastric Ulcer in Adults | 24.65 mga or 49.3 mgb | Once Daily for up to 6 months**
H. pylori Eradication to Reduce the Risk of Duodenal Ulcer Recurrence in Adults
Triple Therapy:
esomeprazole strontium | 49.3 mgb | Once Daily for 10 Days
Amoxicillin | 1000 mg | Twice Daily for 10 Days
Clarithromycin | 500 mg | Twice Daily for 10 Days
Pathological Hypersecretory Conditions Including Zollinger-Ellison Syndrome in Adults | 49.3 mg†b | ‡Twice Daily
*[See Clinical Studies (14.1).] The majority of patients are healed within 4 to 8 weeks. For patients who do not heal after 4 to 8 weeks, an additional 4 to 8 weeks of treatment may be considered.
**Controlled studies did not extend beyond six months.
***If symptoms do not resolve completely after 4 weeks, an additional 4 weeks of treatment may be considered.
†The dosage of esomeprazole strontium in patients with pathological hypersecretory conditions varies with the individual patient. Dosage regimens should be adjusted to individual patient needs.
‡Doses up to 240 mg daily have been administered [see Drug Interactions (7)].
a 24.65 mg of esomeprazole strontium is equivalent to 20 mg of esomeprazole
b 49.3 mg of esomeprazole strontium is equivalent to 40 mg of esomeprazole

Refer to amoxicillin and clarithromycin full prescribing information for Contraindications, Warnings, and dosing in elderly and in renally-impaired patients.

Special Populations

Hepatic Insufficiency

In patients with mild to moderate liver impairment (Child Pugh Classes A and B), no dosage adjustment is necessary. For patients with severe liver impairment (Child Pugh Class C), a dose of 24.65 mg of esomeprazole strontium (equivalent to 20 mg of esomeprazole) should not be exceeded [see Clinical Pharmacology (12.3)].

Administrative Options

Directions for use specific to the route and available methods of administration are presented in Table 2.

Table 2: Administration Options
Administration Options
(See text following table for additional instructions.)
Dosage Form | Route | Options
Delayed-Release Capsules | Oral | Capsule can be swallowed whole. Do not chew or crush; or; Capsule can be opened and granules mixed with applesauce. Do not chew or crush granules.
Delayed-Release Capsules | Nasogastric Tube | Capsule can be opened and the intact granules emptied into a catheter tipped syringe and delivered through the nasogastric tube.

Esomeprazole strontium delayed-release capsules should be swallowed whole. Do not chew or crush capsule.

Alternatively, for patients who have difficulty swallowing capsules, one tablespoon of applesauce can be added to an empty bowl and the esomeprazole strontium delayed-release capsule can be opened, and the granules inside the capsule carefully emptied onto the applesauce. The granules should be mixed with the applesauce and then swallowed immediately: do not store for future use. The applesauce used should not be hot and should be soft enough to be swallowed without chewing. The granules should not be chewed or crushed. If the granules/applesauce mixture is not used in its entirety, the remaining mixture should be discarded immediately.

For patients who have a nasogastric tube in place, esomeprazole strontium delayed-release capsules can be opened and the intact granules emptied into a 60 mL catheter tipped syringe and mixed with 50 mL of water. It is important to only use a catheter tipped syringe when administering esomeprazole strontium delayed-release capsules through a nasogastric tube. Replace the plunger and shake the syringe vigorously for 15 seconds. Hold the syringe with the tip up and check for granules remaining in the tip. Attach the syringe to a nasogastric tube and deliver the contents of the syringe through the nasogastric tube into the stomach. After administering the granules, the nasogastric tube should be flushed with additional water. Do not administer the granules if they have dissolved or disintegrated.

The mixture must be used immediately after preparation.

3 DOSAGE FORMS AND STRENGTHS

Delayed-release capsules: 24.65 mg of esomeprazole strontium (equivalent to 20 mg of esomeprazole) - hard capsules with light pink cap and body containing off white to pale brown granules with HMP 20 printed in black ink.

Delayed-release capsules: 49.3 mg of esomeprazole strontium (equivalent to 40 mg of esomeprazole) - hard capsules with dark pink cap and body containing off white to pale brown granules with HMP 40 printed in black ink.

4 CONTRAINDICATIONS

Esomeprazole strontium is contraindicated in patients with known hypersensitivity to proton pump inhibitors. Hypersensitivity reactions, e.g., angioedema and anaphylactic shock, have been reported with esomeprazole use.

For information about contraindications of antibacterial agents (clarithromycin and amoxicillin) indicated in combination with esomeprazole strontium, refer to the CONTRAINDICATIONS section of their package inserts.

5 WARNINGS AND PRECAUTIONS

5.1 Concurrent Gastric Malignancy

Symptomatic response to therapy with esomeprazole strontium does not preclude the presence of gastric malignancy.

5.2 Atrophic Gastritis

Atrophic gastritis has been noted occasionally in gastric corpus biopsies from patients treated long-term with omeprazole, of which esomeprazole is an enantiomer.

5.3 Clostridium difficile Associated Diarrhea

Published observational studies suggest that PPI therapy like esomeprazole strontium may be associated with an increased risk of Clostridium difficile associated diarrhea, especially in hospitalized patients. This diagnosis should be considered for diarrhea that does not improve [see Adverse Reactions (6.2)].

Patients should use the lowest dose and shortest duration of PPI therapy appropriate to the condition being treated.

Clostridium difficile associated diarrhea (CDAD) has been reported with use of nearly all antibacterial agents. For more information specific to antibacterial agents (clarithromycin and amoxicillin) indicated for use in combination with esomeprazole strontium, refer to WARNINGS and PRECAUTIONS sections of those package inserts.

5.4 Interaction with Clopidogrel

Avoid concomitant use of esomeprazole strontium with clopidogrel. Clopidogrel is a prodrug. Inhibition of platelet aggregation by clopidogrel is entirely due to an active metabolite. The metabolism of clopidogrel to its active metabolite can be impaired by use with concomitant medications, such as esomeprazole, that inhibit CYP2C19 activity. Concomitant use of clopidogrel with 40 mg esomeprazole reduces the pharmacological activity of clopidogrel. When using esomeprazole strontium, consider alternative anti-platelet therapy [see Drug Interactions (7.3) and Clinical Pharmacology (12.3)].

5.5 Bone Fracture

Several published observational studies suggest that proton pump inhibitor (PPI) therapy may be associated with an increased risk for osteoporosis-related fractures of the hip, wrist, or spine. The risk of fracture was increased in patients who received high-dose, defined as multiple daily doses, and long-term PPI therapy (a year or longer). Patients should use the lowest dose and shortest duration of PPI therapy appropriate to the condition being treated. Patients at risk for osteoporosis-related fractures should be managed according to established treatment guidelines [see Dosage and Administration (2) and Adverse Reactions (6.2)].

5.6 Hypomagnesemia

Hypomagnesemia, symptomatic and asymptomatic, has been reported rarely in patients treated with PPIs for at least three months, in most cases after a year of therapy. Serious adverse events include tetany, arrhythmias, and seizures. In most patients, treatment of hypomagnesemia required magnesium replacement and discontinuation of the PPI.

For patients expected to be on prolonged treatment or who take PPIs with medications such as digoxin or drugs that may cause hypomagnesemia (e.g., diuretics), health care professionals may consider monitoring magnesium levels prior to initiation of PPI treatment and periodically [see Adverse Reactions (6.2)].

5.7 Concomitant Use of esomeprazole strontium with St. John’s Wort or Rifampin

Drugs which induce CYP2C19 or CYP3A4 (such as St. John’s Wort or rifampin) can substantially decrease esomeprazole concentrations [see Drug Interactions (7.3)]. Avoid concomitant use of esomeprazole strontium with St. John’s Wort or rifampin.

5.8 Interactions with Diagnostic Investigations for Neuroendocrine Tumors

Serum chromogranin A (CgA) levels increase secondary to drug-induced decreases in gastric acidity. The increased CgA level may cause false positive results in diagnostic investigations for neuroendocrine tumors. Providers should temporarily stop esomeprazole treatment before assessing CgA levels and consider repeating the test if initial CgA levels are high. If serial tests are performed (e.g., for monitoring), the same commercial laboratory should be used for testing, as reference ranges between tests may vary.

5.9 Concomitant Use of esomeprazole strontium with Methotrexate

Literature suggests that concomitant use of PPIs with methotrexate (primarily at high dose; see methotrexate prescribing information) may elevate and prolong serum levels of methotrexate and/or its metabolite, possibly leading to methotrexate toxicities. In high-dose methotrexate administration a temporary withdrawal of the PPI may be considered in some patients [see Drug Interactions (7.7)].

6 ADVERSE REACTIONS

6.1 Clinical Trials Experience

Because clinical trials are conducted under widely varying conditions, adverse reaction rates observed in the clinical trials of a drug cannot be directly compared to rates in the clinical trials of another drug and may not reflect the rates observed in practice.

The safety of esomeprazole strontium has been established from adequate and well-controlled studies of esomeprazole magnesium [see Clinical Studies (14)]. Below is a display of the adverse reactions of esomeprazole magnesium in these adequate and well-controlled studies.

Adults

The safety of esomeprazole magnesium was evaluated in over 15,000 patients (aged 18 to 84 years) in clinical trials worldwide including over 8,500 patients in the United States and over 6,500 patients in Europe and Canada. Over 2,900 patients were treated in long-term studies for up to 6‑12 months. In general, esomeprazole magnesium was well tolerated in both short and long-term clinical trials.

The safety in the treatment of healing of erosive esophagitis was assessed in four randomized comparative clinical trials, which included 1,240 patients on 22.3 mg of esomeprazole magnesium (equivalent to 20 mg of esomeprazole), 2,434 patients on 44.6 mg of esomeprazole magnesium (equivalent to 40 mg of esomeprazole), and 3,008 patients on 20 mg of omeprazole daily. The most frequently occurring adverse reactions (≥1%) in all three groups were headache (5.5%, 5%, and 3.8%, respectively) and diarrhea (no difference among the three groups). Nausea, flatulence, abdominal pain, constipation, and dry mouth occurred at similar rates among patients taking esomeprazole magnesium or omeprazole.

Additional adverse reactions that were reported as possibly or probably related to esomeprazole magnesium with an incidence <1% are listed below by body system:

Body as a Whole: abdomen enlarged, allergic reaction, asthenia, back pain, chest pain, substernal chest pain, facial edema, peripheral edema, hot flushes, fatigue, fever, flu-like disorder, generalized edema, leg edema, malaise, pain, rigors;

Cardiovascular: flushing, hypertension, tachycardia;

Endocrine: goiter;

Gastrointestinal: bowel irregularity, constipation aggravated, dyspepsia, dysphagia, dysplasia GI, epigastric pain, eructation, esophageal disorder, frequent stools, gastroenteritis, GI hemorrhage, GI symptoms not otherwise specified, hiccup, melena, mouth disorder, pharynx disorder, rectal disorder, serum gastrin increased, tongue disorder, tongue edema, ulcerative stomatitis, vomiting;

Hearing: earache, tinnitus;

Hematologic: anemia, anemia hypochromic, cervical lymphadenopathy, epistaxis, leukocytosis, leukopenia, thrombocytopenia;

Hepatic: bilirubinemia, hepatic function abnormal, SGOT increased, SGPT increased;

Metabolic/Nutritional: glycosuria, hyperuricemia, hyponatremia, increased alkaline phosphatase, thirst, vitamin B12 deficiency, weight increase, weight decrease;

Musculoskeletal: arthralgia, arthritis aggravated, arthropathy, cramps, fibromyalgia syndrome, hernia, polymyalgia rheumatica;

Nervous System/Psychiatric: anorexia, apathy, appetite increased, confusion, depression aggravated, dizziness, hypertonia, nervousness, hypoesthesia, impotence, insomnia, migraine, migraine aggravated, paresthesia, sleep disorder, somnolence, tremor, vertigo, visual field defect;

Reproductive: dysmenorrhea, menstrual disorder, vaginitis;

Respiratory: asthma aggravated, coughing, dyspnea, larynx edema, pharyngitis, rhinitis, sinusitis;

Skin and Appendages: acne, angioedema, dermatitis, pruritus, pruritus ani, rash, rash erythematous, rash maculo-papular, skin inflammation, sweating increased, urticaria;

Special Senses: otitis media, parosmia, taste loss, taste perversion;

Urogenital: abnormal urine, albuminuria, cystitis, dysuria, fungal infection, hematuria, micturition frequency, moniliasis, genital moniliasis, polyuria;

Visual: conjunctivitis, vision abnormal.

The following potentially clinically significant laboratory changes in clinical trials, irrespective of relationship to esomeprazole magnesium, were reported in ≤ 1% of patients: increased creatinine, uric acid, total bilirubin, alkaline phosphatase, ALT, AST, hemoglobin, white blood cell count, platelets, serum gastrin, potassium, sodium, thyroxine and thyroid stimulating hormone [see Clinical Pharmacology (12)]. Decreases were seen in hemoglobin, white blood cell count, platelets, potassium, sodium, and thyroxine.

Endoscopic findings that were reported as adverse reactions include: duodenitis, esophagitis, esophageal stricture, esophageal ulceration, esophageal varices, gastric ulcer, gastritis, hernia, benign polyps or nodules, Barrett’s esophagus, and mucosal discoloration.

The incidence of treatment-related adverse reactions during 6-month maintenance treatment was similar to placebo. There were no differences in types of related adverse reactions seen during maintenance treatment up to 12 months compared to short-term treatment.

Two placebo-controlled studies were conducted in 710 patients for the treatment of symptomatic gastroesophageal reflux disease. The most common adverse reactions that were reported as possibly or probably related to esomeprazole magnesium were diarrhea (4.3%), headache (3.8%), and abdominal pain (3.8%).

Combination Treatment with Amoxicillin and Clarithromycin

In clinical trials using combination therapy with esomeprazole magnesium plus amoxicillin and clarithromycin, no additional adverse reactions specific to these drug combinations were observed. Adverse reactions that occurred were limited to those observed when using esomeprazole magnesium, amoxicillin, or clarithromycin alone.

The most frequently reported drug-related adverse reactions for patients who received triple therapy for 10 days were diarrhea (9.2%), taste perversion (6.6%), and abdominal pain (3.7%). No treatment-emergent adverse reactions were observed at higher rates with triple therapy than were observed with esomeprazole magnesium alone.

For more information on adverse reactions with amoxicillin or clarithromycin, refer to their package inserts, Adverse Reactions sections.

In clinical trials using combination therapy with esomeprazole magnesium plus amoxicillin and clarithromycin, no additional increased laboratory abnormalities particular to these drug combinations were observed.

For more information on laboratory changes with amoxicillin or clarithromycin, refer to their package inserts, Adverse Reactions section.

6.2 Postmarketing Experience

The following adverse reactions have been identified during post-approval use of esomeprazole magnesium. Because these reactions are reported voluntarily from a population of uncertain size, it is not always possible to reliably estimate their frequency or establish a causal relationship to drug exposure. These reports are listed below by body system:

Blood and Lymphatic: agranulocytosis, pancytopenia;

Eye: blurred vision;

Gastrointestinal: pancreatitis, stomatitis, microscopic colitis;

Hepatobiliary: hepatic failure, hepatitis with or without jaundice;

Immune System: anaphylactic reaction/shock;

Infections and Infestations: GI candidiasis; Clostridium difficile associated diarrhea;

Metabolism and nutritional disorders: hypomagnesemia;

Musculoskeletal and Connective Tissue: muscular weakness, myalgia, bone fracture;

Nervous System: hepatic encephalopathy, taste disturbance;

Psychiatric: aggression, agitation, depression, hallucination;

Renal and Urinary: interstitial nephritis;

Reproductive System and Breast: gynecomastia;

Respiratory, Thoracic, and Mediastinal: bronchospasm;

Skin and Subcutaneous Tissue: alopecia, erythema multiforme, hyperhidrosis, photosensitivity, Stevens-Johnson syndrome, toxic epidermal necrolysis (some fatal).

7 DRUG INTERACTIONS

7.1 Interference with Antiretroviral Therapy

Concomitant use of atazanavir and nelfinavir with proton pump inhibitors is not recommended. Coadministration of atazanavir with proton pump inhibitors is expected to substantially decrease atazanavir plasma concentrations and may result in a loss of therapeutic effect and the development of drug resistance. Coadministration of saquinavir with proton pump inhibitors is expected to increase saquinavir concentrations, which may increase toxicity and require dose reduction.

Omeprazole, of which esomeprazole is an enantiomer, has been reported to interact with some antiretroviral drugs. The clinical importance and the mechanisms behind these interactions are not always known. Increased gastric pH during omeprazole treatment may change the absorption of the antiretroviral drug. Other possible interaction mechanisms are via CYP2C19.

Reduced concentrations of atazanavir and nelfinavir

For some antiretroviral drugs, such as atazanavir and nelfinavir, decreased serum levels have been reported when given together with omeprazole. Following multiple doses of nelfinavir (1250 mg, twice daily) and omeprazole (40 mg daily), AUC was decreased by 36% and 92%, Cmax by 37% and 89% and Cmin by 39% and 75%, respectively for nelfinavir and M8. Following multiple doses of atazanavir (400 mg, daily) and omeprazole (40 mg, daily, 2 hr before atazanavir), AUC was decreased by 94%, Cmax by 96%, and Cmin by 95%. Concomitant administration with omeprazole and drugs such as atazanavir and nelfinavir is therefore not recommended.

Increased concentrations of saquinavir

For other antiretroviral drugs, such as saquinavir, elevated serum levels have been reported, with an increase in AUC by 82%, in Cmax by 75%, and in Cmin by 106%, following multiple dosing of saquinavir/ritonavir (1000/100 mg) twice daily for 15 days with omeprazole 40 mg daily coadministered days 11 to 15. Therefore, clinical and laboratory monitoring for saquinavir toxicity is recommended during concurrent use with esomeprazole. Dose reduction of saquinavir should be considered from the safety perspective for individual patients.

7.2 Drugs for Which Gastric pH Can Affect Bioavailability

Esomeprazole inhibits gastric acid secretion. Therefore, esomeprazole may interfere with the absorption of drugs where gastric pH is an important determinant of bioavailability. Similar to other drugs that decrease the intragastric acidity, the absorption of drugs such as ketoconazole, atazanavir, iron salts, and erlotinib can decrease, while the absorption of drugs such as digoxin can increase during treatment with esomeprazole. Concomitant treatment with omeprazole (20 mg daily) and digoxin in healthy subjects increased the bioavailability of digoxin by 10% (30% in two subjects). Esomeprazole is an enantiomer of omeprazole. Coadministration of digoxin with esomeprazole is expected to increase the systemic exposure of digoxin. Therefore, patients may need to be monitored when digoxin is taken concomitantly with esomeprazole.

7.3 Effects on Hepatic Metabolism/Cytochrome P-450 Pathways

Esomeprazole is extensively metabolized in the liver by CYP2C19 and CYP3A4. In vitro and in vivo studies have shown that esomeprazole is not likely to inhibit CYPs 1A2, 2A6, 2C9, 2D6, 2E1, and 3A4. No clinically relevant interactions with drugs metabolized by these CYP enzymes would be expected. Drug interaction studies have shown that esomeprazole does not have any clinically significant interactions with phenytoin, quinidine, clarithromycin, or amoxicillin.

Although drug interaction studies have not shown that esomeprazole has a clinically significant interaction with warfarin, post-marketing reports of changes in prothrombin measures have been received among patients on concomitant warfarin and esomeprazole therapy. Increases in INR and prothrombin time may lead to abnormal bleeding and even death. Patients treated with proton pump inhibitors and warfarin concomitantly may need to be monitored for increases in INR and prothrombin time.

Esomeprazole may potentially interfere with CYP2C19, the major esomeprazole metabolizing enzyme. Coadministration of esomeprazole 30 mg and diazepam, a CYP2C19 substrate, resulted in a 45% decrease in clearance of diazepam.

Clopidogrel is metabolized to its active metabolite in part by CYP2C19. Concomitant use of esomeprazole 40 mg results in reduced plasma concentrations of the active metabolite of clopidogrel and a reduction in platelet inhibition. Avoid concomitant administration of esomeprazole strontium with clopidogrel. When using esomeprazole strontium, consider use of alternative anti-platelet therapy [see Clinical Pharmacology (12.3)].

Omeprazole acts as an inhibitor of CYP2C19. Omeprazole, given in doses of 40 mg daily for one week to 20 healthy subjects in cross-over study, increased Cmax and AUC of cilostazol by 18% and 26% respectively. Cmax and AUC of one of its active metabolites, 3,4-dihydrocilostazol, which has 4- 7 times the activity of cilostazol, were increased by 29% and 69% respectively. Coadministration of cilostazol with esomeprazole is expected to increase concentrations of cilostazol and its above mentioned active metabolite. Therefore a dose reduction of cilostazol from 100 mg twice daily to 50 mg twice daily should be considered.

Concomitant administration of esomeprazole and a combined inhibitor of CYP2C19 and CYP3A4, such as voriconazole, may result in more than doubling of the esomeprazole exposure. Dose adjustment of esomeprazole is not normally required. However, in patients with Zollinger-Ellison’s Syndrome, who may require higher doses up to 240 mg/day, dose adjustment may be considered.

Drugs known to induce CYP2C19 or CYP3A4 or both (such as rifampin) may lead to decreased esomeprazole serum levels. Omeprazole, of which esomeprazole is an enantiomer, has been reported to interact with St. John’s Wort, an inducer of CYP3A4. In a cross-over study in 12 healthy male subjects, St. John’s Wort (300 mg three times daily for 14 days) significantly decreased the systemic exposure of omeprazole in CYP2C19 poor metabolisers (Cmax and AUC decreased by 37.5% and 37.9%, respectively) and extensive metabolisers (Cmax and AUC decreased by 49.6 % and 43.9%, respectively). Avoid concomitant use of St. John’s Wort or rifampin with esomeprazole strontium.

7.4 Interactions with Investigations of Neuroendocrine Tumors

Drug-induced decrease in gastric acidity results in enterochromaffin-like cell hyperplasia and increased Chromogranin A levels, which may interfere with investigations for neuroendocrine tumors [see Warnings and Precautions (5.7) and Clinical Pharmacology (12.2)].

7.5 Tacrolimus

Concomitant administration of esomeprazole and tacrolimus may increase the serum levels of tacrolimus.

7.6 Combination Therapy with Clarithromycin

Coadministration of esomeprazole, clarithromycin, and amoxicillin has resulted in increases in the plasma levels of esomeprazole and 14-hydroxyclarithromycin [see Clinical Pharmacology (12.4)].

Concomitant administration of clarithromycin with other drugs can lead to serious adverse reactions due to drug interactions [see Warnings and Precautions in prescribing information for clarithromycin]. Because of these drug interactions, clarithromycin is contraindicated for coadministration with certain drugs [see Contraindications in prescribing information for clarithromycin].

7.7 Methotrexate

Case reports, published population pharmacokinetic studies, and retrospective analyses suggest that concomitant administration of PPIs and methotrexate (primarily at high dose; see methotrexate prescribing information) may elevate and prolong serum levels of methotrexate and/or its metabolite hydroxymethotrexate. However, no formal drug interaction studies of methotrexate with PPIs have been conducted [see Warnings and Precautions (5.9)].

8 USE IN SPECIFIC POPULATIONS

8.1 Pregnancy

Pregnancy Category C

Risk Summary

There are no adequate and well controlled studies of esomeprazole strontium delayed-release capsules in pregnant women. Teratogenicity was not observed in an embryofetal developmental study in rats with either esomeprazole strontium or esomeprazole magnesium at equimolar oral doses up to 280 mg esomeprazole/kg/day (about 57 times the daily maximum recommended human dose (MRHD) of 40 mg on a body surface area basis). When administered as either the strontium or magnesium salt, changes in bone morphology and physeal dysplasia were observed in pre- and postnatal developmental toxicity studies in rats at doses equal to or greater than 138 mg esomeprazole/kg/day (approximately 33.6 times the daily MRHD of 40 mg on a body surface area basis). Because of the observed effect at the high doses of esomeprazole strontium on developing bone in rat studies, esomeprazole strontium should be used during pregnancy only if the potential benefit justifies the potential risk to the fetus.

Animal Data

An embryofetal developmental (teratogenicity) study in rats was performed with both esomeprazole strontium and esomeprazole magnesium at equimolar oral doses of 14 to 280 mg esomeprazole/kg/day (about 3.4 to 57 times the daily maximum recommended human dose (MRHD) of 40 mg, on a body surface area basis). At the doses tested, there were no teratogenic or adverse effects on general fetal development or on fetal visceral or skeletal structures. In addition, there was no adverse effect on maternal and fetal bone calcium levels when esomeprazole was administered as either the strontium or magnesium salt. Fetal exposure to strontium and esomeprazole was dose-related.

Pre- and postnatal developmental toxicity studies in rats with additional endpoints to evaluate bone development were performed with both esomeprazole strontium and esomeprazole magnesium at equimolar oral doses of 14 to 280 mg esomeprazole/kg/day (about 3.4 to 57 times the daily MRHD of 40 mg of esomeprazole on a body surface area basis). The rats were fed either a standard diet or a diet with reduced levels of calcium and Vitamin D. When administered as either the strontium or magnesium salt, neonatal/early postnatal (birth to weaning) survival was decreased, body weight and body weight gain were reduced and neurobehavioral or general developmental delays in the immediate post-weaning timeframe were evident at doses equal to or greater than 69 mg esomeprazole/kg/day (about 16.8 times the daily MRHD of 40 mg on a body surface area basis). In addition, when administered as either the strontium or magnesium salt, decreased femur length, width and thickness of cortical bone, decreased thickness of the tibial growth plate and minimal to mild bone marrow hypocellularity were noted at doses equal to or greater than 14 mg esomeprazole/kg/day (about 3.4 times the MRHD of 40 mg on a body surface area basis). Physeal dysplasia in the femur was observed in offspring of rats treated with oral doses of esomeprazole (as either the strontium or the magnesium salt) at doses equal to or greater than 138 mg/kg/day (about 33.6 times the daily MRHD of 40 mg on a body surface area basis). No significant differences were observed between the groups fed nutritionally complete diet and those fed the diet with reduced levels of calcium and Vitamin D.

Adverse effects on maternal bone were observed in pregnant and lactating rats in the pre- and postnatal toxicity studies when esomeprazole strontium or esomeprazole magnesium were administered at equimolar oral doses of 14 to 280 mg esomeprazole/kg/day (about 3.4 to 57 times the daily MRHD of 40 mg on a body surface area basis). When rats were dosed from gestational day 7 through weaning on postnatal day 21, a statistically significant decrease in maternal femur weight of up to 14% (as compared to placebo treatment) was observed at doses equal to or greater than 138 mg esomeprazole/kg/day (about 33.6 times the daily MRHD of 40 mg on a body surface area basis).

8.3 Nursing Mothers

Limited published data indicate that esomeprazole and strontium are present in human milk. Because of the effect of esomeprazole strontium observed at high doses on developing bone in rat studies, a decision should be made whether to discontinue nursing or to discontinue the drug, taking into account the importance of the drug to the mother [see Use in Specific Populations (8.1)].

8.4 Pediatric Use

The safety and effectiveness of esomeprazole strontium delayed-release capsules have not been established in pediatric patients. Strontium is known to compete with calcium for intestinal absorption and is incorporated into bone. Therefore, use in pediatric patients is not recommended because adequate safety studies have not been performed.

In a juvenile rat toxicity study, following administration of either esomeprazole strontium or esomeprazole magnesium at equimolar oral doses of 140 to 280 mg esomeprazole/kg/day (34 to 57 times the daily MRHD of 40 mg on a body surface area basis), increases in deaths were seen at the high dose, along with treatment-related decreases in body weight and body weight gain, decreases in femur weight and femur length and decreases in overall growth [see Nonclinical Toxicology (13.2)].

Symptomatic GERD in infants less than one year of age

A pediatric study of esomeprazole magnesium did not establish efficacy for symptomatic GERD in patients less than 1 year of age. A multicenter, randomized, double-blind, placebo-controlled, treatment-withdrawal study of 98 patients ages 1 to 11 months, inclusive, with symptomatic GERD did not demonstrate a difference between esomeprazole magnesium and placebo.

8.5 Geriatric Use

Of the total number of patients who received esomeprazole magnesium in clinical trials, 1459 were 65 to 74 years of age and 354 patients were ≥75 years of age.

No overall differences in safety and efficacy were observed between the elderly and younger individuals, and other reported clinical experience has not identified differences in responses between the elderly and younger patients, but greater sensitivity of some older individuals cannot be ruled out.

8.6 Use in Patients with Renal Impairment

No dosage adjustment is necessary in patients with mild to moderate renal impairment. The pharmacokinetics and safety of strontium in patients with severe renal impairment has not been studied and, therefore, use in this patient population is not recommended.

10 OVERDOSAGE

A single oral dose of esomeprazole at 510 mg/kg (about 103 times the human dose on a body surface area basis), was lethal to rats. The major signs of acute toxicity were reduced motor activity, changes in respiratory frequency, tremor, ataxia, and intermittent clonic convulsions.

The symptoms described in connection with deliberate esomeprazole overdose (limited experience of doses in excess of 240 mg/day) are transient. Single doses of 80 mg of esomeprazole were uneventful. Reports of overdosage with omeprazole in humans may also be relevant. Doses ranged up to 2,400 mg (120 times the usual recommended clinical dose). Manifestations were variable, but included confusion, drowsiness, blurred vision, tachycardia, nausea, diaphoresis, flushing, headache, dry mouth, and other adverse reactions similar to those seen in normal clinical experience (see omeprazole package insert - Adverse Reactions). No specific antidote for esomeprazole is known. Since esomeprazole is extensively protein bound, it is not expected to be removed by dialysis. In the event of overdosage, treatment should be symptomatic and supportive.

As with the management of any overdose, the possibility of multiple drug ingestion should be considered. For current information on treatment of any drug overdose contact a Poison Control Center at 1-800-222-1222.

11 DESCRIPTION

The active ingredient in the proton pump inhibitor esomeprazole strontium delayed-release capsules is bis(5‑ methoxy-2-[(S)-[(4-methoxy-3,5-dimethyl-2-pyridinyl)methyl]sulfinyl]-1H-benzimidazole-1-yl) strontium tetrahydrate. Esomeprazole is the S-isomer of omeprazole, which is a mixture of the S- and R- isomers. The molecular formula of esomeprazole strontium is (C17H18N3O3S)2·Sr·4H2O with molecular weight of 848.50. The structural formula is:

Figure 1

The strontium salt is a white or almost white crystalline powder. Each molecule contains 4 moles of water of solvation and is soluble in water.

Esomeprazole strontium is supplied in delayed-release capsules. Each delayed-release capsule contains 24.65 mg esomeprazole strontium equivalent to 20 mg esomeprazole or 49.3 mg esomeprazole strontium equivalent to 40 mg esomeprazole, in the form of enteric-coated granules with the following inactive ingredients: calcium carbonate, hypromellose, methacrylic acid copolymer dispersion, mono- and diglycerides, polysorbate 80, sugar spheres, talc, triethyl citrate. The 24.65 mg capsule shells have the following inactive ingredients: gelatin, titanium dioxide, synthetic iron oxide. The 49.3 mg capsule shells have the following inactive ingredients: gelatin, titanium dioxide, FD&C Blue #1, FD&C Red #40, FD&C Yellow #6.

Each 24.65 mg capsule contains 2.6 mg of strontium. Each 49.3 mg capsule contains 5.1 mg of strontium.

12 CLINICAL PHARMACOLOGY

12.1 Mechanism of Action

Esomeprazole is a proton pump inhibitor that suppresses gastric acid secretion by specific inhibition of the H^+/K^+-ATPase in the gastric parietal cell. The S- and R-isomers of omeprazole are protonated and converted in the acidic compartment of the parietal cell forming the active inhibitor, the achiral sulphenamide. By acting specifically on the proton pump, esomeprazole blocks the final step in acid production, thus reducing gastric acidity. This effect is dose-related up to a daily dose of 20 to 40 mg and leads to inhibition of gastric acid secretion.

12.2 Pharmacodynamics

Antisecretory Activity

The effect of esomeprazole magnesium on intragastric pH was determined in patients with symptomatic gastroesophageal reflux disease in two separate studies. In the first study of 36 patients, 44.6 mg of esomeprazole magnesium (equivalent to 40 mg of esomeprazole) and 22.3 mg of esomeprazole magnesium (equivalent to 20 mg of esomeprazole) were administered over 5 days. The results are shown in Table 3:

Table 3: Effect on Intragastric pH on Day 5 (N=36)
Parameter | esomeprazole magnesium 44.6 mg | esomeprazole magnesium 22.3 mg
% Time Gastric pH >4† (Hours) | 70%* (16.8 h) | 53% (12.7 h)
Coefficient of variation | 26% | 37%
Median 24 Hour pH | 4.9* | 4.1
Coefficient of variation | 16% | 27%
†Gastric pH was measured over a 24-hour period.
*p< 0.01 esomeprazole magnesium 44.6 mg vs. esomeprazole magnesium 22.3 mg

In a second study, the effect on intragastric pH of esomeprazole magnesium 44.6 mg administered once daily over a five-day period was similar to the first study, (% time with pH >4 was 68% or 16.3 hours).

Serum Gastrin Effects

The effect of esomeprazole magnesium on serum gastrin concentrations was evaluated in approximately 2,700 patients in clinical trials up to 8 weeks and in over 1,300 patients for up to 6 to 12 months. The mean fasting gastrin level increased in a dose-related manner. This increase reached a plateau within two to three months of therapy and returned to baseline levels within four weeks after discontinuation of therapy.

Increased gastrin causes enterochromaffin-like cell hyperplasia and increased serum Chromogranin A (CgA) levels. The increased CgA levels may cause false positive results in diagnostic investigations for neuroendocrine tumors.

Enterochromaffin-like (ECL) Cell Effects

In 24-month carcinogenicity studies of omeprazole in rats, a dose-related significant occurrence of gastric ECL cell carcinoid tumors and ECL cell hyperplasia was observed in both male and female animals [see Nonclinical Toxicology (13.1)]. Carcinoid tumors have also been observed in rats subjected to fundectomy or long-term treatment with other proton pump inhibitors or high doses of H2-receptor antagonists.

Human gastric biopsy specimens have been obtained from more than 3,000 patients treated with omeprazole in long-term clinical trials. The incidence of ECL cell hyperplasia in these studies increased with time; however, no case of ECL cell carcinoids, dysplasia, or neoplasia has been found in these patients.

In over 1,000 patients treated with esomeprazole magnesium (10, 20, or 40 mg/day) up to 6 to 12 months, the prevalence of ECL cell hyperplasia increased with time and dose. No patient developed ECL cell carcinoids, dysplasia, or neoplasia in the gastric mucosa.

Endocrine Effects

Esomeprazole magnesium had no effect on thyroid function when given in oral doses of 22.3 mg or 44.6 mg for 4 weeks. Other effects of esomeprazole on the endocrine system were assessed using omeprazole studies. Omeprazole given in oral doses of 30 or 40 mg for 2 to 4 weeks had no effect on carbohydrate metabolism, circulating levels of parathyroid hormone, cortisol, estradiol, testosterone, prolactin, cholecystokinin, or secretin.

12.3 Pharmacokinetics

Absorption

Following single oral administration of esomeprazole strontium delayed-release capsules 49.3 mg (equivalent to 40 mg of esomeprazole) in 36 healthy adults under fasting conditions, the peak plasma concentrations (Cmax) of esomeprazole occurred at approximately 1.7 hours post-dose. Mean esomeprazole Cmax and area under the plasma concentration‑time curve (AUC) were comparable to those for esomeprazole magnesium delayed-release capsules 44.6 mg (equivalent to 40 mg of esomeprazole). In a study using esomeprazole magnesium delayed-release capsules, esomeprazole Cmax increased proportionally when the dose was increased, and there was a three‑fold increase in esomeprazole AUC when the dose was increased from 22.3 mg (equivalent to 20 mg of esomeprazole) to 44.6 mg. Systemic bioavailability will increase following multiple dosing and esomeprazole AUC is expected to increase to approximately 2.6‑fold after once daily dosing of esomeprazole strontium delayed-release capsules 49.3 mg for 5 days.

In one single dose study in 39 healthy adult subjects under fasting conditions, the capsule contents of esomeprazole strontium delayed-release capsules 49.3 mg were sprinkled onto one tablespoon of applesauce, mean esomeprazole Cmax and AUC were comparable to those for esomeprazole magnesium delayed-release capsules 44.6 mg administered under the same conditions. In a food-effect study, the AUC after administration of a single 49.3 mg dose of esomeprazole strontium delayed-release capsules decreased by 52% after a high fat meal compared to fasting conditions. Esomeprazole strontium delayed-release capsules should be taken at least one hour before meals.

Table 4: Pharmacokinetic Parameters of Esomeprazole Following Single Oral Administration in Healthy Adult Volunteers under Fasting Conditions
Parameters | Esomeprazole strontium delayed-release capsules 49.3 mg |  | Esomeprazole strontium delayed-release capsules 49.3 mg (with one tablespoon of apple saucea)
Parameters | Meanb | SD | Meanb | SD
Cmax (ng/mL) | 1105.6 | 464.8 | 1155.6 | 429.8
Tmax (h) | 1.7 |  | 2.3
AUC0-tlast (ng*h/Ml) | 2283.9 | 1400.4 | 2389.1 | 1071.4
AUC0-∞ (ng*h/mL) | 2310.9 | 1428.3 | 2417.8 | 1081.8
aCapsule contents were administered with one tablespoon of applesauce under otherwise fasting conditions.
bValues represent the arithmetic mean, except Tmax, which is the median.

Distribution

Esomeprazole is 97% bound to plasma proteins. Plasma protein binding is constant over the concentration range of 2 to 20 μmol/L. The apparent volume of distribution at steady-state in healthy volunteers is approximately 16 L.

Metabolism

Esomeprazole is extensively metabolized in the liver by the cytochrome P450 (CYP) enzyme system. The metabolites of esomeprazole lack antisecretory activity. The major part of esomeprazole’s metabolism is dependent upon the CYP2C19 isoenzyme, which forms the hydroxy and desmethyl metabolites. The remaining amount is dependent on CYP3A4 which forms the sulphone metabolite. CYP2C19 isoenzyme exhibits polymorphism in the metabolism of esomeprazole, since some 3% of Caucasians and 15 to 20% of Asians lack CYP2C19 and are termed Poor Metabolizers. At steady state, the ratio of AUC in Poor Metabolizers to AUC in the rest of the population (Extensive Metabolizers) is approximately 2.

Following administration of equimolar doses, the S- and R-isomers are metabolized differently by the liver, resulting in higher plasma levels of the S- than of the R-isomer.

Excretion

The plasma elimination half-life of esomeprazole is approximately 1 to 1.5 hours. Less than 1% of parent drug is excreted in the urine. Approximately 80% of an oral dose of esomeprazole is excreted as inactive metabolites in the urine, and the remainder is found as inactive metabolites in the feces.

Combination Therapy with Antimicrobials

Esomeprazole magnesium 44.6 mg once daily was given in combination with clarithromycin 500 mg twice daily and amoxicillin 1000 mg twice daily for 7 days to 17 healthy male and female subjects. The mean steady-state AUC and Cmax of esomeprazole increased by 70% and 18%, respectively, during triple combination therapy compared to treatment with esomeprazole alone. The observed increase in esomeprazole exposure during coadministration with clarithromycin and amoxicillin is not expected to produce significant safety concerns.

The pharmacokinetic parameters for clarithromycin and amoxicillin were similar during triple combination therapy and administration of each drug alone. However, the mean AUC and Cmax for 14-hydroxyclarithromycin increased by 19% and 22%, respectively, during triple combination therapy compared to treatment with clarithromycin alone. This increase in exposure to 14-hydroxyclarithromycin is not considered to be clinically significant.

Concomitant Use with Clopidogrel

Results from a crossover study in healthy subjects have shown a pharmacokinetic interaction between clopidogrel (300 mg loading dose/75 mg daily maintenance dose) and esomeprazole magnesium 44.6 mg p.o. once daily) when co-administered for 30 days. Exposure to the active metabolite of clopidogrel was reduced by 35% to 40% over this time period. Pharmacodynamic parameters were also measured and demonstrated that the change in inhibition of platelet aggregation was related to the change in the exposure to clopidogrel active metabolite.

Special Populations

Geriatric

The esomeprazole AUC and Cmax values were slightly higher (25% and 18%, respectively) in the elderly as compared to younger subjects after administration of esomeprazole magnesium to steady state. Dosage adjustment based on age is not necessary.

Gender

The esomeprazole AUC and Cmax values were slightly higher (13%) in females than in males after administration of esomeprazole magnesium to steady state. Dosage adjustment based on gender is not necessary.

Hepatic Insufficiency

The steady state pharmacokinetics of esomeprazole obtained after administration of esomeprazole magnesium 44.6 mg once daily to 4 patients each with mild (Child Pugh A), moderate (Child Pugh Class B), and severe (Child Pugh Class C) liver insufficiency were compared to those obtained in 36 male and female GERD patients with normal liver function. In patients with mild and moderate hepatic insufficiency, the esomeprazole AUCs were within the range that could be expected in patients with normal liver function. In patients with severe hepatic insufficiency the AUCs were 2 to 3 times higher than in the patients with normal liver function. No dosage adjustment is recommended for patients with mild to moderate hepatic insufficiency (Child Pugh Classes A and B). However, in patients with severe hepatic insufficiency (Child Pugh Class C) esomeprazole strontium dose of 24.65 mg once daily should not be exceeded [see Dosage and Administration (2)].

Renal Insufficiency

The pharmacokinetics of esomeprazole in patients with renal impairment are not expected to be altered relative to healthy volunteers as less than 1% of esomeprazole is excreted unchanged in urine. In a study with a different strontium product and dose in patients with mild to moderate renal impairment, strontium clearance was reduced with the decrease in creatinine clearance. The pharmacokinetics of strontium in patients with severe renal impairment has not been characterized [see Use in Specific Populations (8.6)].

Other pharmacokinetic observations

Coadministration of oral contraceptives, diazepam, phenytoin, or quinidine did not seem to change the pharmacokinetic profile of esomeprazole.

Studies evaluating concomitant administration of esomeprazole magnesium and either naproxen (non-selective NSAID) or rofecoxib (COX-2 selective NSAID) did not identify any clinically relevant changes in the pharmacokinetic profiles of esomeprazole or these NSAIDs.

12.4 Microbiology

Esomeprazole, amoxicillin, and clarithromycin triple therapy has been shown to be active against most strains of Helicobacter pylori (H. pylori) in vitro and in clinical infections [see Indications and Usage (1) and Clinical Studies (14)].

Helicobacter pylori: Susceptibility testing of H. pylori isolates was performed for amoxicillin and clarithromycin using agar dilution methodology, and minimum inhibitory concentrations (MICs) were determined.

Pretreatment Resistance: Clarithromycin pretreatment resistance rate (MIC ≥1 mcg/mL) to H. pylori was 15% (66/445) at baseline in all treatment groups combined. A total of >99% (394/395) of patients had H. pylori isolates that were considered to be susceptible (MIC ≤0.25 mcg/mL) to amoxicillin at baseline. One patient had a baseline H. pylori isolate with an amoxicillin MIC = 0.5 mcg/mL.

Clarithromycin Susceptibility Test Results and Clinical/Bacteriologic Outcomes: The baseline H. pylori clarithromycin susceptibility results and the H. pylori eradication results at the Day 38 visit are shown in Table 5:

Table 5: Clarithromycin Susceptibility Test Results and Clinical/Bacteriological Outcomesa for Triple Therapy - (esomeprazole magnesium 44.6 mg# once daily/amoxicillin 1000 mg twice daily/clarithromycin 500 mg twice daily for 10 days)
Clarithromycin Pretreatment Results | H. pylori negative (Eradicated) | H. pylori positive (Not Eradicated) Post-treatment susceptibility results
Clarithromycin Pretreatment Results | H. pylori negative (Eradicated) | Sb | Ib | Rb | No MIC
Susceptibleb 182 | 162 | 4 | 0 | 2 | 14
Intermediateb 1 | 1 | 0 | 0 | 0 | 0
Resistantb 29 | 13 | 1 | 0 | 13 | 2
aIncludes only patients with pretreatment and post-treatment clarithromycin susceptibility test results
bSusceptible (S) MIC ≤0.25 mcg/mL, Intermediate (I) MIC = 0.5 mcg/mL, Resistant (R) MIC ≥1.0 mcg/mL
# 44.6 mg of esomeprazole magnesium is equivalent to 40 mg of esomeprazole

Patients not eradicated of H. pylori following esomeprazole magnesium/amoxicillin/clarithromycin triple therapy will likely have clarithromycin resistant H. pylori isolates. Therefore, clarithromycin susceptibility testing should be done, when possible. Patients with clarithromycin resistant H. pylori should not be re-treated with a clarithromycin-containing regimen.

Amoxicillin Susceptibility Test Results and Clinical/Bacteriological Outcomes:

In the esomeprazole magnesium/amoxicillin/clarithromycin clinical trials, 83% (176/212) of the patients in the esomeprazole magnesium/amoxicillin/clarithromycin treatment group who had pretreatment amoxicillin susceptible MICs (≤0.25 mcg/mL) were eradicated of H. pylori, and 17% (36/212) were not eradicated of H. pylori. Of the 36 patients who were not eradicated of H. pylori on triple therapy, 16 had no post-treatment susceptibility test results and 20 had post-treatment H. pylori isolates with amoxicillin susceptible MICs. Fifteen of the patients who were not eradicated of H. pylori on triple therapy also had post-treatment H. pylori isolates with clarithromycin resistant MICs. There were no patients with H. pylori isolates who developed treatment emergent resistance to amoxicillin.

Susceptibility Test for Helicobacter pylori: For susceptibility testing information about Helicobacter pylori, see Microbiology section in prescribing information for clarithromycin and amoxicillin.

Effects on Gastrointestinal Microbial Ecology: Decreased gastric acidity due to any means, including proton pump inhibitors, increases gastric counts of bacteria normally present in the gastrointestinal tract. Treatment with proton pump inhibitors may lead to slightly increased risk of gastrointestinal infections such as Salmonella and Campylobacter and possibly Clostridium difficile in hospitalized patients.

13 NONCLINICAL TOXICOLOGY

13.1 Carcinogenesis, Mutagenesis, Impairment of Fertility

The carcinogenic potential of esomeprazole was assessed using studies of omeprazole, of which esomeprazole is an enantiomer. In two 24-month oral carcinogenicity studies in rats, omeprazole at daily doses of 1.7, 3.4, 13.8, 44, and 141 mg/kg/day (about 0.7 to 57 times the human dose of 20 mg/day expressed on a body surface area basis) produced gastric ECL cell carcinoids in a dose-related manner in both male and female rats; the incidence of this effect was markedly higher in female rats, which had higher blood levels of omeprazole. Gastric carcinoids seldom occur in the untreated rat. In addition, ECL cell hyperplasia was present in all treated groups of both sexes. In one of these studies, female rats were treated with 13.8 mg omeprazole/kg/day (about 5.6 times the human dose on a body surface area basis) for 1 year, then followed for an additional year without the drug. No carcinoids were seen in these rats. An increased incidence of treatment-related ECL cell hyperplasia was observed at the end of 1 year (94% treated vs. 10% controls). By the second year the difference between treated and control rats was much smaller (46% vs. 26%) but still showed more hyperplasia in the treated group. Gastric adenocarcinoma was seen in one rat (2%). No similar tumor was seen in male or female rats treated for 2 years. For this strain of rat no similar tumor has been noted historically, but a finding involving only one tumor is difficult to interpret. A 78-week mouse carcinogenicity study of omeprazole did not show increased tumor occurrence, but the study was not conclusive.

Esomeprazole strontium was negative in the Ames mutation test, in the in vivo rat bone marrow cell chromosome aberration test, and the in vivo mouse micronucleus test. Esomeprazole magnesium, however, was positive in the in vitro human lymphocyte chromosome aberration test. Omeprazole was positive in the in vitro human lymphocyte chromosome aberration test, the in vivo mouse bone marrow cell chromosome aberration test, and the in vivo mouse micronucleus test.

The potential effects of esomeprazole strontium on fertility and reproductive performance were not directly studied. Omeprazole at oral doses up to 138 mg/kg/day in rats (about 33.6 times the daily MRHD of 40 mg on a body surface area basis) was found to have no effect on reproductive performance of parental animals.

13.2 Animal Toxicology and/or Pharmacology

A 28-day toxicity study with a 14-day recovery phase was conducted in juvenile rats with esomeprazole strontium or esomeprazole magnesium at equimolar oral doses of 70 to 280 mg esomeprazole/kg/day (about 17 to 57 times the daily MRHD of 40 mg on a body surface area basis). When administered as either the strontium or magnesium salt from postnatal day 7 through postnatal day 35, the dose of 280 mg esomeprazole/kg/day produced an increase in the number of deaths. In addition, when administered as either the strontium or magnesium salt, doses equal to or greater than 140 mg esomeprazole/kg/day (about 34 times the daily MRHD of 40 mg on a body surface area basis) produced treatment-related decreases in body weight (approximately 14%) and body weight gain, decreases in femur weight and femur length, and affected overall growth.

14 CLINICAL STUDIES

The safety and efficacy of esomeprazole strontium has been established based on adequate and well-controlled adult studies of esomeprazole magnesium in the healing and maintenance of erosive esophagitis, symptomatic GERD, risk reduction of NSAID-associated gastric ulcer, H. pylori eradication to reduce the risk of duodenal ulcer recurrence, and pathological hypersecretory conditions including Zollinger-Ellison Syndrome. Below is a display of the results of the adequate and well-controlled studies of esomeprazole magnesium in these conditions.

14.1 Healing of Erosive Esophagitis

The healing rates of 44.6 mg of esomeprazole magnesium (equivalent to 40 mg of esomeprazole), 22.3 mg of esomeprazole magnesium (equivalent to 20 mg of esomeprazole), and 20 mg of omeprazole (the approved dose for this indication) were evaluated in patients with endoscopically diagnosed erosive esophagitis in four multicenter, double-blind, randomized studies. The healing rates at Weeks 4 and 8 were evaluated and are shown in Table 6:

Table 6: Erosive Esophagitis Healing Rate (Life-Table Analysis)

Study | No. of Patients | Treatment Groups | Week 4 | Week 8 | Significance Level*
1 | 588 | Esomeprazole magnesium 22.3 mg | 68.7% | 90.6% | N.S.
 | 588 | Omeprazole 20 mg | 69.5% | 88.3%
2 | 654 | Esomeprazole magnesium 44.6 mg | 75.9% | 94.1% | p < 0.001
 | 656 | Esomeprazole magnesium 22.3 mg | 70.5% | 89.9% | p < 0.05
 | 650 | Omeprazole 20 mg | 64.7% | 86.9%
3 | 576 | Esomeprazole magnesium 44.6 mg | 71.5% | 92.2% | N.S.
 | 572 | Omeprazole 20 mg | 68.6% | 89.8%
4 | 1216 | Esomeprazole magnesium 44.6 mg | 81.7% | 93.7% | p < 0.001
 | 1209 | Omeprazole 20 mg | 68.7% | 84.2%
*log-rank test vs. omeprazole 20 mg
N.S. = not significant (p >0.05)

In these same studies of patients with erosive esophagitis, sustained heartburn resolution and time to sustained heartburn resolution were evaluated and are shown in Table 7:

Table 7: Sustained Resolution‡ of Heartburn (Erosive Esophagitis Patients)

 |  |  | Cumulative Percent#with Sustained Resolution
Study | No. of Patients | Treatment Groups | Day 14 | Day 28 | Significance Level*
1 | 573 | Esomeprazole magnesium 22.3 mg | 64.3% | 72.7% | N.S.
1 | 555 | Omeprazole 20 mg | 64.1% | 70.9%
2 | 621 | Esomeprazole magnesium 44.6 mg | 64.8% | 74.2% | p <0.001
2 | 620 | Esomeprazole magnesium 22.3 mg | 62.9% | 70.1% | N.S.
2 | 626 | Omeprazole 20 mg | 56.5% | 66.6%
3 | 568 | Esomeprazole magnesium 44.6 mg | 65.4% | 73.9% | N.S.
3 | 551 | Omeprazole 20 mg | 65.5% | 73.1%
4 | 1187 | Esomeprazole magnesium 44.6 mg | 67.6% | 75.1% | p <0.001
4 | 1188 | Omeprazole 20 mg | 62.5% | 70.8%
‡Defined as 7 consecutive days with no heartburn reported in daily patient diary.
#Defined as the cumulative proportion of patients who have reached the start of sustained resolution
*log-rank test vs omeprazole 20 mg
N.S. = not significant (p > 0.05)

In these four studies, the range of median days to the start of sustained resolution (defined as 7 consecutive days with no heartburn) was 5 days for esomeprazole magnesium 44.6 mg, 7 to 8 days for esomeprazole magnesium 22.3 mg and 7 to 9 days for omeprazole 20 mg.

There are no comparisons of 44.6 mg of esomeprazole magnesium with 40 mg of omeprazole in clinical trials assessing either healing or symptomatic relief of erosive esophagitis.

Long-Term Maintenance of Healing of Erosive Esophagitis

Two multicenter, randomized, double-blind placebo-controlled 4-arm trials were conducted in patients with endoscopically confirmed, healed erosive esophagitis to evaluate esomeprazole magnesium 44.6 mg (n=174), 22.3 mg (n=180), 11.15 mg (n=168) or placebo (n=171) once daily over six months of treatment.

No additional clinical benefit was seen with esomeprazole magnesium 44.6 mg over esomeprazole magnesium 22.3 mg.

The percentages of patients that maintained healing of erosive esophagitis at the various time points are shown in the Figures 2 and 3:

Figure 2: Maintenance of Healing Rates by Month (Study 177) - Esomeprazole Magnesium

s = scheduled visit

Figure 3: Maintenance of Healing Rates by Month (Study 178) - Esomeprazole Magnesium

s= scheduled visit

Patients remained in remission significantly longer and the number of recurrences of erosive esophagitis was significantly less in patients treated with esomeprazole magnesium compared to placebo.

In both studies, the proportion of patients on esomeprazole magnesium who remained in remission and were free of heartburn and other GERD symptoms was well differentiated from placebo.

In a third multicenter open label study of 808 patients treated for 12 months with esomeprazole magnesium 44.6 mg, the percentage of patients that maintained healing of erosive esophagitis was 93.7% for six months and 89.4% for one year.

14.2 Symptomatic Gastroesophageal Reflux Disease (GERD)

Two multicenter, randomized, double-blind, placebo-controlled studies were conducted in a total of 717 patients comparing four weeks of treatment with 22.3 mg or 44.6 mg of esomeprazole magnesium (equivalent to 20 mg or 40 mg of esomeprazole, respectively) once daily versus placebo for resolution of GERD symptoms. Patients had ≥ 6-month history of heartburn episodes, no erosive esophagitis by endoscopy, and heartburn on at least four of the seven days immediately preceding randomization.

The percentage of patients that were symptom-free of heartburn was significantly higher in the esomeprazole magnesium groups compared to placebo at all follow-up visits (Weeks 1, 2, and 4).

No additional clinical benefit was seen with esomeprazole magnesium 44.6 mg over esomeprazole magnesium 22.3 mg.

The percent of patients symptom-free of heartburn by day are shown in the Figures 4 and 5:

Figure 4: Percent of Patients Symptom-Free of Heartburn by Day (Study 225) - Esomeprazole Magnesium

Figure 5: Percent of Patients Symptom-Free of Heartburn by Day (Study 226) - Esomeprazole Magnesium

In three European symptomatic GERD trials, esomeprazole magnesium 22.3 mg and 44.6 mg and omeprazole 20 mg were evaluated. No significant treatment related differences were seen.

14.3 Risk Reduction of NSAID-Associated Gastric Ulcer

Two multicenter, double-blind, placebo-controlled studies were conducted in patients at risk of developing gastric and/or duodenal ulcers associated with continuous use of non-selective and COX-2 selective NSAIDs. A total of 1429 patients were randomized across the 2 studies. Patients ranged in age from 19 to 89 (median age 66.0 years) with 70.7% female, 29.3% male, 82.9% Caucasian, 5.5% Black, 3.7% Asian, and 8% Others. At baseline, the patients in these studies were endoscopically confirmed not to have ulcers but were determined to be at risk for ulcer occurrence due to their age (≥60 years) and/or history of a documented gastric or duodenal ulcer within the past 5 years. Patients receiving NSAIDs and treated with 22.3 mg or 44.6 mg of esomeprazole magnesium (equivalent to 20 mg or 40 mg of esomeprazole, respectively) once a day experienced significant reduction in gastric ulcer occurrences relative to placebo treatment at 26 weeks. See Table 8. No additional benefit was seen with esomeprazole magnesium 44.6 mg over esomeprazole magnesium 22.3 mg. These studies did not demonstrate significant reduction in the development of NSAID-associated duodenal ulcer. The incidence of duodenal ulcers in these trials was low.

Table 8: Cumulative Percentage of Patients without Gastric Ulcers at 26 Weeks
Study | No. of Patients | Treatment Group | % of Patients Remaining Gastric Ulcer Free*
1 | 191 | esomeprazole magnesium 22.3 mg | 95.4
 | 194 | esomeprazole magnesium 44.6 mg | 96.7
 | 184 | Placebo | 88.2
2 | 267 | esomeprazole magnesium 22.3 mg | 94.7
 | 271 | esomeprazole magnesium 44.6 mg | 95.3
 | 257 | Placebo | 83.3
* %=Life Table Estimate. Significant difference from placebo (p<0.01).

14.4 Helicobacter pylori (H. pylori) Eradication in Patients with Duodenal Ulcer Disease

Triple Therapy (esomeprazole magnesium/amoxicillin/clarithromycin): Two multicenter, randomized, double-blind studies were conducted using a 10 day treatment regimen. The first study (191) compared 44.6 mg of esomeprazole magnesium (equivalent to 40 mg of esomeprazole) once daily in combination with amoxicillin 1000 mg twice daily and clarithromycin 500 mg twice daily to 44.6 mg of esomeprazole magnesium once daily plus clarithromycin 500 mg twice daily. The second study (193) compared 44.6 mg of esomeprazole magnesium once daily in combination with amoxicillin 1000 mg twice daily and clarithromycin 500 mg twice daily to 44.6 mg of esomeprazole magnesium once daily. H. pylori eradication rates, defined as at least two negative tests and no positive tests from CLOtest®, histology and/or culture at 4 weeks post-therapy, were significantly higher in the esomeprazole magnesium plus amoxicillin and clarithromycin group than in the esomeprazole magnesium plus clarithromycin or esomeprazole magnesium alone group. The results are shown in Table 9:

Table 9: H. pylori Eradication Rates at 4 Weeks after 10 Day Treatment Regimen
% of Patients Cured
[95% Confidence Interval]
(Number of Patients)
Study | Treatment Group | Per-Protocol† | Intent-to-Treat‡
191 | esomeprazole magnesium plus amoxicillin and clarithromycin | 84%* [78, 89] (n=196) | 77%* [71, 82] (n=233)
191 | esomeprazole magnesium plus clarithromycin | 55% [48, 62] (n=187) | 52% [45, 59] (n=215)
193 | esomeprazole magnesium plus amoxicillin and clarithromycin | 85%** [74, 93] (n=67) | 78%** [67, 87] (n=74)
193 | esomeprazole magnesium | 5% [0, 23] (n=22) | 4% [0, 21] (n=24)
†Patients were included in the analysis if they had H. pylori infection documented at baseline, had at least one endoscopically verified duodenal ulcer ≥0.5 cm in diameter at baseline or had a documented history of duodenal ulcer disease within the past 5 years, and were not protocol violators. Patients who dropped out of the study due to an adverse reaction related to the study drug were included in the analysis as not H. pylori eradicated.
‡Patients were included in the analysis if they had documented H. pylori infection at baseline, had at least one documented duodenal ulcer at baseline, or had a documented history of duodenal ulcer disease, and took at least one dose of study medication. All dropouts were included as not H. pylori eradicated.
*p < 0.05 compared to esomeprazole magnesium plus clarithromycin
**p < 0.05 compared to esomeprazole magnesium alone

The percentage of patients with a healed baseline duodenal ulcer by 4 weeks after the 10 day treatment regimen in the esomeprazole magnesium plus amoxicillin and clarithromycin group was 75% (n=156) and 57% (n=60) respectively, in the studies 191 and 193 (per-protocol analysis).

14.5 Pathological Hypersecretory Conditions Including Zollinger-Ellison Syndrome

In a multicenter, open-label dose-escalation study of 21 patients (15 males and 6 females, 18 Caucasian and Black, mean age of 55.5 years) with pathological hypersecretory conditions, such as Zollinger-Ellison Syndrome, esomeprazole magnesium significantly inhibited gastric acid secretion. Initial dose was 44.6 mg of esomeprazole magnesium (equivalent to 40 mg of esomeprazole) twice daily in 19/21 patients and 89.2 mg of esomeprazole magnesium (equivalent to 80 mg of esomeprazole) twice daily in 2/21 patients. Total daily esomeprazole magnesium doses ranging from 89.2 mg to 267.6 mg (equivalent to 240 mg of esomeprazole) for 12 months maintained gastric acid output below the target levels of 10 mEq/h in patients without prior gastric acid-reducing surgery and below 5 mEq/hr in patients with prior gastric acid-reducing surgery. At the Month 12 final visit, 18/20 (90%) patients had Basal Acid Output (BAO) under satisfactory control (median BAO = 0.17 mmol/hr). Of the 18 patients evaluated with a starting dose of 40 mg twice daily, 13 (72%) had their BAO controlled with the original dosing regimen at the final visit. See Table 10.

Table 10: Adequate Acid Suppression at Final Visit by Dose Regimen
Esomeprazole magnesium dose at the Month 12 visit | BAO under adequate control at the Month 12 visit (N=20)*
44.6 mg twice daily | 13/15
89.2 mg twice daily | 4/4
89.2 mg three times daily | 1/1
*One patient was not evaluated.

16 HOW SUPPLIED/STORAGE AND HANDLING

Esomeprazole strontium delayed-release capsules, 24.65 mg (equivalent to 20 mg of esomeprazole), are hard capsules with light pink cap and body containing off-white to pale brown granules with HMP 20 printed in black ink.

They are available as follows:
Unit of use bottles of 30 NDC 53746-955-03

Esomeprazole strontium delayed-release capsules, 49.3 mg (equivalent to 40 mg of esomeprazole), are hard capsules with dark pink cap and body containing off-white to pale brown granules with HMP 40 printed in black ink.

They are available as follows:
Unit of use bottles of 30 NDC 53746-957-03

Store at 20° to 25°C (68° to 77°F); excursions permitted to 15° to 30°C (59° to 86°F) [See USP Controlled Room Temperature]. Keep esomeprazole strontium delayed-release capsules container tightly closed. Dispense in a tight container if the esomeprazole strontium delayed-release capsules product package is subdivided.

17 PATIENT COUNSELING INFORMATION

See FDA-Approved Patient Labeling (Medication Guide)

- Advise patients to let you know if they are taking, or begin taking, other medications, because esomeprazole strontium delayed-release capsules can interfere with antiretroviral drugs and drugs that are affected by gastric pH changes [see Drug Interactions (7.1)].
- Advise patients to let you know if they have kidney or liver disease [see Use in Specific Populations (8.6), see Clinical Pharmacology (12.3)].
- Let patients know that antacids may be used while taking esomeprazole strontium delayed-release capsules.
- Advise patients to take esomeprazole strontium delayed-release capsules at least one hour before a meal.
- For patients who are prescribed esomeprazole strontium delayed-release capsules, advise them not to chew or crush the capsules.
- Advise patients that, if they open esomeprazole strontium delayed-release capsules to mix the granules with food, the granules should only be mixed with applesauce. Use with other foods has not been evaluated and is not recommended.
- For patients who are advised to open the esomeprazole strontium delayed-release capsules before taking them, instruct them in the proper technique for administration [see Dosage and Administration (2)] and tell them to follow the dosing instructions in the PATIENT INFORMATION insert included in the package.
- Advise patients to immediately report and seek care for diarrhea that does not improve. This may be a sign of Clostridium difficile associated diarrhea [see Warnings and Precautions (5.3)].
- Advise patients to immediately report and seek care for any cardiovascular or neurological symptoms including palpitations, dizziness, seizures, and tetany as these may be signs of hypomagnesemia [see Warnings and Precautions (5.6)].

Licensed from:
Hanmi Pharm. Co. Ltd., Seoul, Korea

Distributed by:
Amneal Pharmaceuticals
Glasgow, KY 42141

MEDICATION GUIDE

ESOMEPRAZOLE STRONTIUM (es-o-mep-ra-zol stron-tee-um)

delayed-release capsules

Read the Medication Guide that comes with esomeprazole strontium before you start taking esomeprazole strontium and each time you get a refill. There may be new information. This information does not take the place of talking with your doctor about your medical condition or your treatment.

What is the most important information I should know about esomeprazole strontium?

Esomeprazole strontium may help your acid-related symptoms, but you could still have serious stomach problems. Talk with your doctor.

Esomeprazole strontium can cause serious side effects, including:

- Diarrhea. Esomeprazole strontium may increase your risk of getting severe diarrhea. This diarrhea may be caused by an infection (Clostridium difficile) in your intestines.

Call your doctor right away if you have watery stool, stomach pain, and fever that does not go away.

- Bone fractures. People who take multiple daily doses of Proton Pump Inhibitor medicines for a long period of time (a year or longer) may have an increased risk of fractures of the hip, wrist, or spine. You should take esomeprazole strontium exactly as prescribed, at the lowest dose possible for your treatment and for the shortest time needed. Talk to your doctor about your risk of bone fracture if you take esomeprazole strontium.

Esomeprazole strontium can have other serious side effects. See “What are the possible side effects of esomeprazole strontium?”

What is esomeprazole strontium?

Esomeprazole strontium is a prescription medicine called a proton pump inhibitor (PPI).
Esomeprazole strontium reduces the amount of acid in your stomach.

Esomeprazole strontium is used in adults:

- for 4 to 8 weeks to treat the symptoms of gastroesophageal reflux disease (GERD). Esomeprazole strontium may also be prescribed to heal acid-related damage to the lining of the esophagus (erosive esophagitis), and to help continue this healing.
  GERD happens when acid in your stomach backs up into the tube (esophagus) that connects your mouth to your stomach. This may cause a burning feeling in your chest or throat, sour taste, or burping.
- for up to 6 months to reduce the risk of stomach ulcers in some people taking pain medicines called non-steroidal anti-inflammatory drugs (NSAIDs)
- to treat patients with a stomach infection (Helicobacter pylori), along with the antibiotics amoxicillin and clarithromycin
- for the long-term treatment of conditions where your stomach makes too much acid, including Zollinger-Ellison Syndrome. Zollinger-Ellison Syndrome is a rare condition in which the stomach produces a more than normal amount of acid.

It is not known if esomeprazole strontium is safe and effective in children. Esomeprazole strontium should not be used in children.

Who should not take esomeprazole strontium?

Do not take esomeprazole strontium if you:

- are allergic to esomeprazole strontium or any of the ingredients in esomeprazole strontium. See the end of this Medication Guide for a complete list of ingredients in esomeprazole strontium.
- are allergic to any other Proton Pump Inhibitor (PPI) medicine

What should I tell my doctor before taking esomeprazole strontium?

Before you take esomeprazole strontium, tell your doctor if you:

- have been told that you have low magnesium levels in your blood
- have liver problems
- have kidney problems. You should not take esomeprazole strontium if you have severe kidney problems.
- have any other medical conditions
- are pregnant or plan to become pregnant. It is not known if esomeprazole strontium can harm your unborn baby.
- are breastfeeding or planning to breastfeed. Esomeprazole strontium passes into your breast milk. You and your doctor should decide if you will take esomeprazole strontium or breastfeed. You should not do both. Talk to your doctor about the best way to feed your baby if you take esomeprazole strontium.

Tell your doctor about all of the medicines you take, including prescription and non-prescription drugs, vitamins and herbal supplements. Esomeprazole strontium may affect how other medicines work, and other medicines may affect how esomeprazole strontium works.

Especially tell your doctor if you take:

- warfarin (Coumadin, Jantoven)
- ketoconazole (Nizoral)
- voriconazole (Vfend)
- atazanavir (Reyataz)
- nelfinavir (Viracept)
- saquinavir (Fortovase)
- products that contain iron
- digoxin (Lanoxin)
- St.John’s Wort (Hypericum perforatum)
- rifampin (Rimactane, Rifater, Rifamate)
- cilostazol (Pletal)
- diazepam (Valium)
- tacrolimus (Prograf)
- erlotinib (Tarceva)
- methotrexate
- clopidogrel (Plavix)

How should I take esomeprazole strontium?

- Take esomeprazole strontium exactly as prescribed by your doctor.
- Do not change your dose or stop esomeprazole strontium without talking to your doctor.
- Take esomeprazole strontium at least 1 hour before a meal.
- Swallow esomeprazole strontium delayed-release capsules whole. Never chew or crush esomeprazole strontium delayed-release capsules.
- If you have difficulty swallowing esomeprazole strontium, you may open the capsule and empty the contents into a tablespoon of applesauce. Esomeprazole strontium should only be mixed with applesauce. The applesauce should not be hot, and it should be soft enough so that you can swallow it without chewing. Mix the contents with the applesauce. Do not crush or chew the granules. Be sure to swallow the applesauce right away. Do not store it for later use.
- If you take too much esomeprazole strontium, call your doctor or local poison control center right away, or go to the nearest hospital emergency room.
- See the “Instructions for Use” at the end of this Medication Guide for instructions about how to mix and give esomeprazole strontium through a nasogastric tube.

What are the possible side effects of esomeprazole strontium?

Esomeprazole strontium can cause serious side effects, including:

- See “What is the most important information I should know about esomeprazole strontium?”
- Chronic (lasting a long time) inflammation of the stomach lining (Atrophic Gastritis). Using esomeprazole strontium for a long period of time may increase the risk of inflammation to your stomach lining. You may or may not have symptoms. Tell your doctor if you have stomach pain, nausea, vomiting, or weight loss.
- Low magnesium levels in your body. This problem can be serious. Low magnesium can happen in some people who take a proton pump inhibitor medicine for at least 3 months. If low magnesium levels happen, it is usually after a year of treatment. You may or may not have symptoms of low magnesium.

Tell your doctor right away if you have any of these symptoms:

- seizures
- dizziness
- abnormal or fast heart beat
- jitteriness
- jerking movements or shaking (tremors)
- muscle weakness
- spasms of the hands and feet
- cramps or muscle aches
- spasm of the voice box

Your doctor may check the level of magnesium in your body before you start taking esomeprazole strontium or during treatment if you will be taking esomeprazole strontium for a long period of time.

The most common side effects with esomeprazole strontium may include:

- headache
- diarrhea
- nausea
- gas
- abdominal pain
- constipation
- dry mouth

Other side effects:

Serious allergic reactions. Tell your doctor if you get any of the following symptoms with esomeprazole strontium:

- rash
- face swelling
- throat tightness
- difficulty breathing

Your doctor may stop esomeprazole strontium if these symptoms happen.

Tell your doctor if you have any side effects that bother you or that do not go away. These are not all the possible side effects with esomeprazole strontium.

Call your doctor for medical advice about side effects. You may report side effects to FDA at 1-800-FDA-1088.

How should I store esomeprazole strontium?

- Store esomeprazole strontium at room temperature between 68°F to 77°F (20°C to 25°C).
- Keep the container of esomeprazole strontium closed tightly.

Keep esomeprazole strontiumand all medicines out of the reach of children.

General information about esomeprazole strontium

Medicines are sometimes prescribed for purposes other than those listed in a Medication Guide. Do not use esomeprazole strontium for a condition for which it was not prescribed. Do not give esomeprazole strontium to other people, even if they have the same symptoms you have. It may harm them.

This Medication Guide summarizes the most important information about esomeprazole strontium. If you would like more information, talk with your doctor. You can ask your pharmacist or doctor for information about esomeprazole strontium that is written for health professionals.

For more information, go to www.amneal.com or call 1-877-835-5472.

What are the ingredients in esomeprazole strontium?

Active ingredient: esomeprazole strontium tetrahydrate

Inactive ingredients:calcium carbonate, hypromellose, methacrylic acid copolymer dispersion, mono- and diglycerides, polysorbate 80, sugar spheres, talc, triethyl citrate.

The 24.65 mg capsule shells contain: gelatin, titanium dioxide, synthetic iron oxide.

The 49.3 mg capsule shells contain: gelatin, titanium dioxide, FD&C Blue #1, FD&C Red #40, FD&C Yellow #6.

Instructions for Use

For instructions on taking esomeprazole strontium delayed-release capsules, see the section of this Medication Guide called “How should I take esomeprazole strontium?”

Esomeprazole strontium delayed-release capsules may be given through a nasogastric tube (NG tube) as prescribed by your doctor. Follow the instructions below:

- Open the capsule and empty the granules into a 60 mL catheter tipped syringe. Mix with 50 mL of water. Use only a catheter tipped syringe to give esomeprazole strontium through a NG tube.
- Replace the plunger and shake the syringe well for 15 seconds. Hold the syringe with the tip up and check for granules in the tip.
- Give the medicine right away.
- Do not give the granules if they have dissolved or have broken into pieces.
- Attach the syringe to the NG tube. Give the medicine in the syringe through the NG tube into the stomach.
- After giving the granules, flush the NG tube with more water.

This Medication Guide has been approved by the U.S. Food and Drug Administration.

Amneal Pharmaceuticals, Glasgow, KY 42141

Issued: August 2013